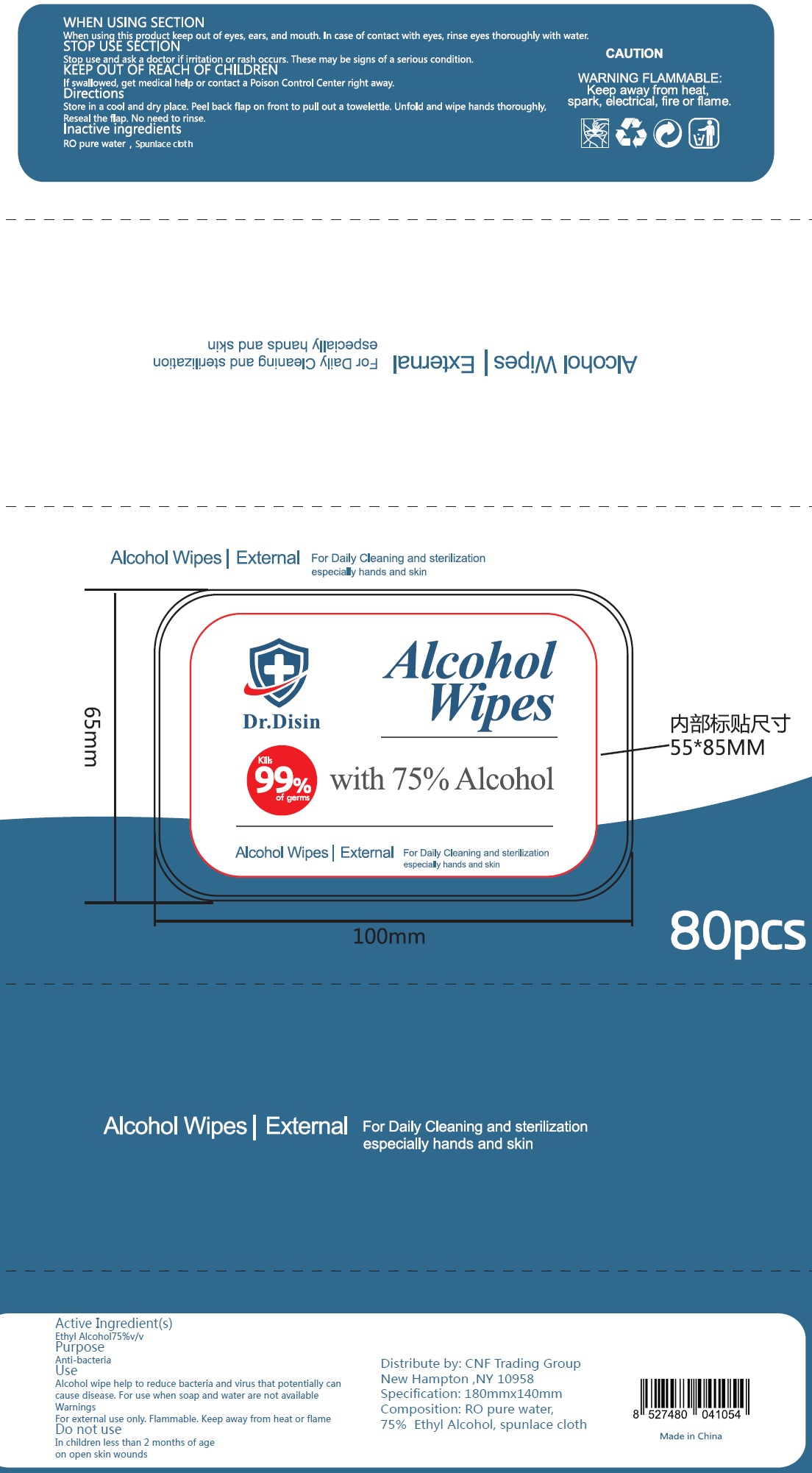 DRUG LABEL: Dr. Disin Alcohol Wipes
NDC: 79205-002 | Form: CLOTH
Manufacturer: CNF Trading Group
Category: otc | Type: HUMAN OTC DRUG LABEL
Date: 20200821

ACTIVE INGREDIENTS: ALCOHOL 0.75 mL/1 mL
INACTIVE INGREDIENTS: WATER

Dr. Disin Alcohol Wipes

Active ingredient [s]

Alcohol 75% v/v

Purpose

Anti-bacteria

Use

Alcohol wipe help to reduce bacteria and virus that potentially can cause disease. For use when soap and water are not available

Warnings:

For external use only. Flammable, Keep away from heat or flame.

Do not use:

In children less than 2 months of age. On open skin wounds.

When using this product:

keep out of eyes, ears, and mouth. In case of contact with eyes, rinse eyes thoroughly with water.

Stop Use and ask a doctor:

if irritation or rash occur, These may be signs of a serious condition.

KEEP OUT OF REACH OF CHILDREN

If swallowed, get medical help or contact a Poison Control Center right away.

Directions:

Store in a cool and dry place. Peel back flap on front to pull out a towelettle. Unfold and wipe hands thoroughly, Reseal the flap. No need to rinse.

Inactive ingredients

RO pure water, spunlace cloth